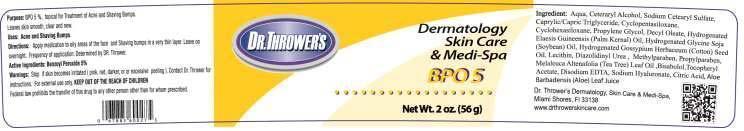 DRUG LABEL: DR. THROWERS BPO 5
NDC: 69299-103 | Form: CREAM
Manufacturer: DR. THROWER'S SKINCARE, INC.
Category: prescription | Type: HUMAN PRESCRIPTION DRUG LABEL
Date: 20150522

ACTIVE INGREDIENTS: BENZOYL PEROXIDE 5 g/100 g
INACTIVE INGREDIENTS: WATER; CETOSTEARYL ALCOHOL; SODIUM CETOSTEARYL SULFATE; MEDIUM-CHAIN TRIGLYCERIDES; CYCLOMETHICONE 5; CYCLOMETHICONE 6; PROPYLENE GLYCOL; DECYL OLEATE; HYDROGENATED PALM KERNEL OIL; HYDROGENATED SOYBEAN OIL; HYDROGENATED COTTONSEED OIL; LECITHIN, SOYBEAN; DIAZOLIDINYL UREA; METHYLPARABEN; PROPYLPARABEN; TEA TREE OIL; .ALPHA.-BISABOLOL, (+)-; .ALPHA.-TOCOPHEROL ACETATE; EDETATE DISODIUM; HYALURONATE SODIUM; ANHYDROUS CITRIC ACID; ALOE VERA LEAF

DIRECTIONS:

APPLY MEDICATION TO OILY AREAS OF THE FACE AND SHAVING BUMPS IN A VERY THIN LAYER. LEAVE ON OVERNIGHT. FREQUENCY OF APPLICATION: DETERMINED BY DR. THROWER.

USES:

ACNE AND SHAVING BUMPS.

INGREDIENTS:

Aqua, Ceteraryl Alcohol, Sodium Cetearyl Sulfate, Caprylic/Capric Triglyceride,Cyclopentasiloxane, Cyclohexasiloxane, Propylene Glycol, Decyl Oleate, Hydrogenated Elaesis Guineensis (Palm Kernal) Oil, Hydrogenated Glycine Soja (Soybean) Oil, Hydrogenated Gossypium Herbaceum (Cotton) Seed Oil, Lecithin, Diazolidinyl Urea, Methylparaben, Propylparaben, MELALEUCA ALTERNIFOLIA (TEA TREE) LEAF OIL, BISABOLOL, Tocopheryl Acetate, Disodium EDTA, Sodium Hyaluronate, Citric Acid, Aloe Barbadensis (Aloe) Leaf Juice

WARNINGS

STOP IF SKIN BECOMES IRRITATED (PINK, RED DARKER, OR EXCESSIVE PEELING). COTACT DR. THROWER FOR INSTRUCTIONS. FOR EXTERNAL USE ONLY. KEEP OUT OF REACH OF CHILDREN. FEDERAL LAW PROHIBITS THE TRANSFER OF THIS DRUG TO ANY OTHER PERSON OTHER THAN FOR WHOM IT IS PRESCRIBED.